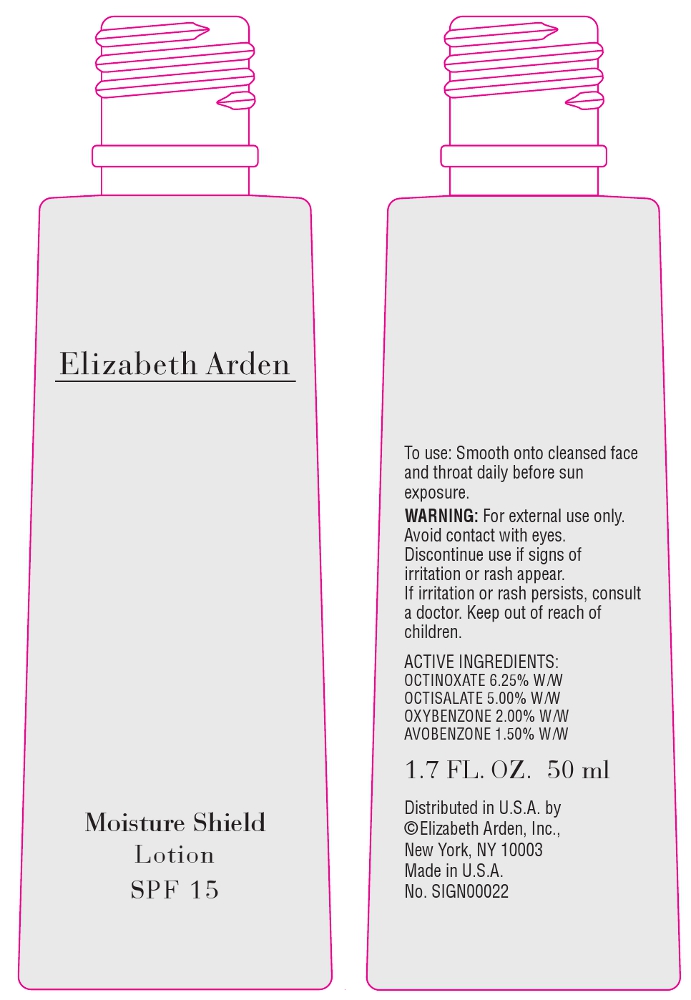 DRUG LABEL: Elizabeth Arden Moisture Shield SPF 15
NDC: 67938-0801 | Form: LOTION
Manufacturer: Elizabeth Arden, Inc
Category: otc | Type: HUMAN OTC DRUG LABEL
Date: 20110803

ACTIVE INGREDIENTS: OCTINOXATE 3.125 mL/50 mL; OCTISALATE 2.5 mL/50 mL; OXYBENZONE 1 mL/50 mL; AVOBENZONE 0.75 mL/50 mL
INACTIVE INGREDIENTS: WATER; GLYCERIN; PHENYL TRIMETHICONE; BUTYLENE GLYCOL; PHENOXYETHANOL; PETROLATUM; SHEA BUTTER; CUCUMBER JUICE; LACTIC ACID; ARGININE; CARNOSINE; GLYCINE; LYSINE; PROLINE; PROPYLENE GLYCOL; TREHALOSE; UREA; SUCROSE; STEARIC ACID; XANTHAN GUM; SODIUM SULFITE; BUTYLPHENYL METHYLPROPIONAL; BENZOIC ACID; BUTYLPARABEN; ETHYLPARABEN; ISOBUTYLPARABEN; METHYLPARABEN; POTASSIUM SORBATE; PROPYLPARABEN; SODIUM BENZOATE; CHLORPHENESIN

BB0801

DESCRIPTION

This lightweight, moisturizing lotion provides the ideal level of hydration as it shields skin from the damaging effects of UV rays. Skin feels restored and rebalanced, and looks healthy and glowing.

INDICATIONS AND USAGE

To Use: Smooth on to face before sun exposure.

WARNINGS

Warning: For external use only. Avoid contact with eyes. Discontinue use if signs of irritation or rash appear. If irritation or rash persists, consult a doctor. Keep out of reach of children.

OTC - ACTIVE INGREDIENT

Active Ingredients: Octinoxate 6.25% W/W, Octisalate 5.00% W/W, Oxybenzone 2.00% W/W, Avobenzone 1.50% W/W.

INACTIVE INGREDIENT

Other Ingredients: Water/Aqua/Eau, Cyclopentasiloxane, Isostearyl Neopentanoate, Hydrogenated Polyisobutene, Glycerin, Phenyl Trimethicone, Butylene Glycol, Dimethicone/Vinyl Dimethicone Crosspolymer, Phenoxyethanol, Petrolatum, PEG-8, Theobroma Cacao (Cocoa) Seed Butter, Butyrospermum Parkii (Shea Butter) Extract, Phospholipids, Pentaerythrityl Tetraethylhexanoate, Cucumis Sativus (Cucumber) Juice, Lycium Chinese Fruit Extract, Panax Ginseng Root Extract, Salvia Officinalis (Sage) Leaf Extract, Vanilla Tahitensis Fruit Extract, Sodium Hyaluronate, Lactic Acid, Tocopheryl Acetate, Arginine, Carnosine, Glycine, Lysine, Proline, Propylene Glycol, Sodium PCA, Trehalose, Urea, Hydrogenated Lecithin, Polyphosphorylcholine Glycol Acrylate, Sucrose, Cetearyl Alcohol, Stearic Acid, Polyquaternium-51, Ethoxydiglycol, Acrylates/C10-30 Alkyl Acrylate Crosspolymer, Carbomer, Xanthan Gum, Citric Acid, Triethanolamine, Sodium Sulfite, Disodium EDTA, Hydroxypropyl Starch Phosphate, Dimethiconol, Parfum/Fragrance, Butylene Methylpropional, Limonene, Benzoic Acid, Butylparaben, Ethylparaben, Isobutylparaben, Methylparaben, Potassium Sorbate, Propylparaben, Sodium Benzoate, Chlorphensin.

DOSAGE & ADMINISTRATION

Smooth on to face.

OTC - KEEP OUT OF REACH OF CHILDREN

Keep out of reach of children.

OTC - PURPOSE

Provides SPF 15 sun protection.

OTC - WHEN USING

Avoid contact with eyes.